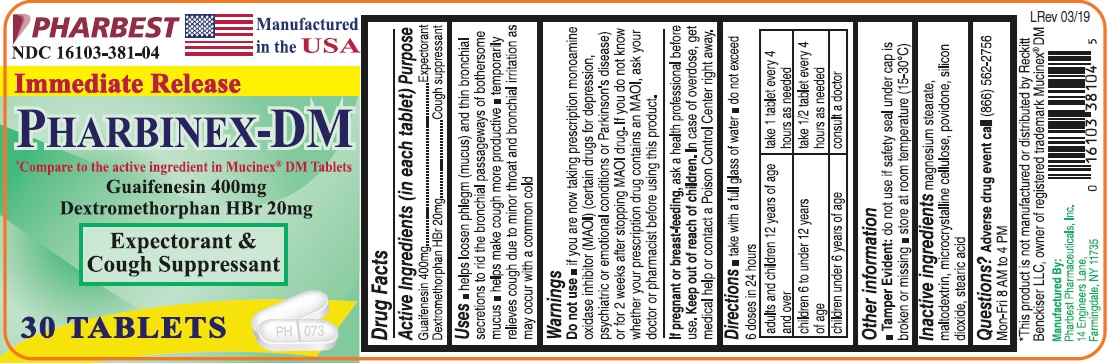 DRUG LABEL: PHARBINEX-DM
NDC: 16103-381 | Form: TABLET
Manufacturer: Pharbest Pharmaceuticals, Inc.
Category: otc | Type: HUMAN OTC DRUG LABEL
Date: 20251224

ACTIVE INGREDIENTS: GUAIFENESIN 400 mg/1 1; DEXTROMETHORPHAN HYDROBROMIDE 20 mg/1 1
INACTIVE INGREDIENTS: MAGNESIUM STEARATE; MALTODEXTRIN; CELLULOSE, MICROCRYSTALLINE; POVIDONE, UNSPECIFIED; SILICON DIOXIDE; STEARIC ACID

Pharbinex DM Tablet

Active ingredients (in each tablet)

Guaifenesin 400mg

Dextromethorphan HBr 20mg

Purpose

Expectorant

Cough suppressant

Uses

- helps loosen phlegm (mucus) and thin bronchial secretions to rid the bronchial passageways of bothersome mucus
- helps make cough more productive
- temporarily relieves cough due to minor throat and bronchial irritation as may occur with a common cold

Warnings

Do not use

- if you are now taking a prescription Monoamine Oxidase Inhibitor (MAOI)(certain drugs for depression, psychiatric or emotional conditions or Parkinson's disease) or for 2 weeks after stopping MAOI drug. If you do not know whether your prescription drug contains MAOI, ask your doctor or pharmacist before using this product.

If pregnant or breast-feeding,

ask a health professional before use.

Keep out of reach of children.

In case of overdose, get medical help or contact a Poison Control Center right away.

Directions

- take with a full glass of water
- do not exceed 6 doses in 24 hours

adults and children 12 years of age and over | take 1 tablet every 4 hours as needed
children 6 to under 12 years of age | take ½ tablet every 4 hours as needed
children under 6 years of age | consult a doctor

Other information

- store at room temperature (15°-30°C)
- Tamper Evident: do not use if safety seal under cap is broken or missing

Inactive ingredients

magnesium stearate, maltodextrin, microcrystalline celluclose, povidone, silicon dioxide, stearic acid.

Questions?

Adverse drug event call (866) 562-2756 Mon-Fri 8 AM to 4 PM

PACKAGE LABEL

PHARBEST

NDC 16103-381-04

Manufactured in the USA

Immediate Release

PHARBINEX-DM

*Compare to the active ingredient in MUCINEX® DM Tablets

Guaifenesin 400mg

Dextromethorphan HBr 20mg

Expectorant &

Cough Suppressant

30 TABLETS